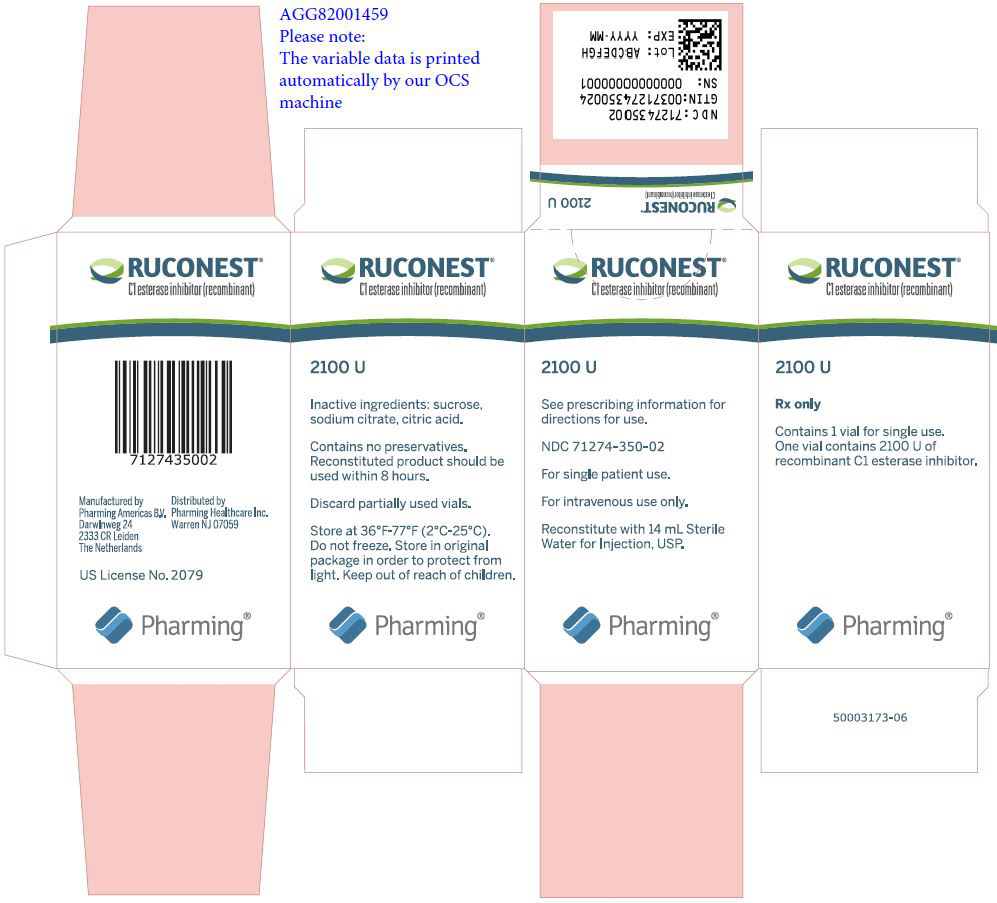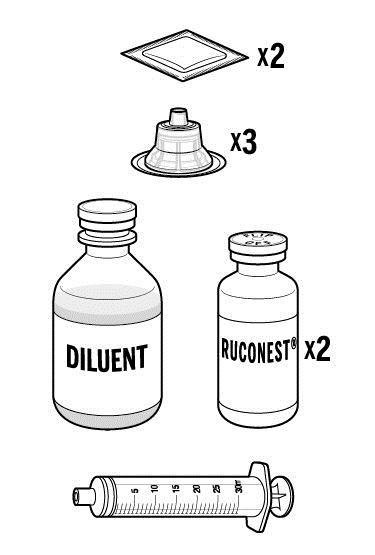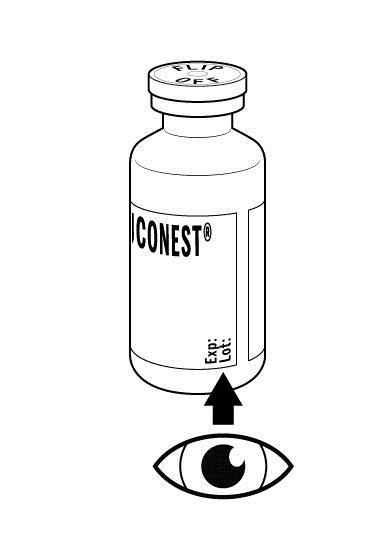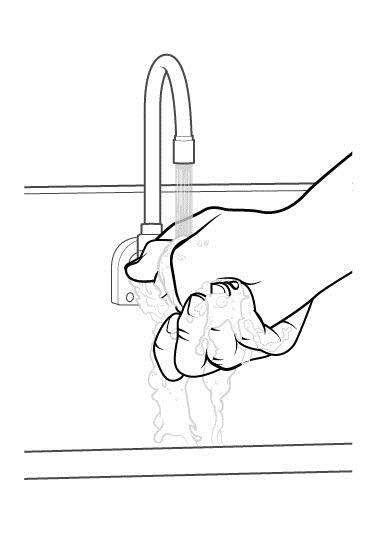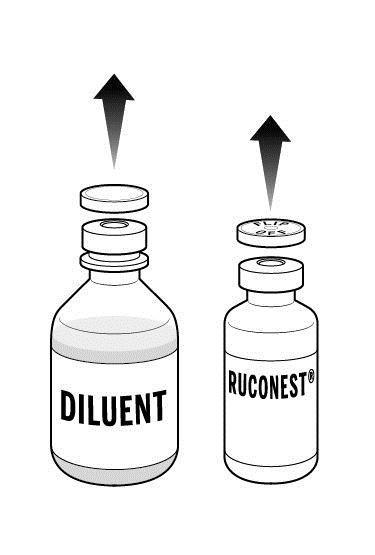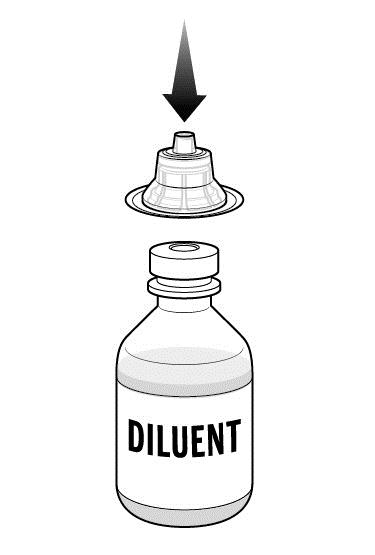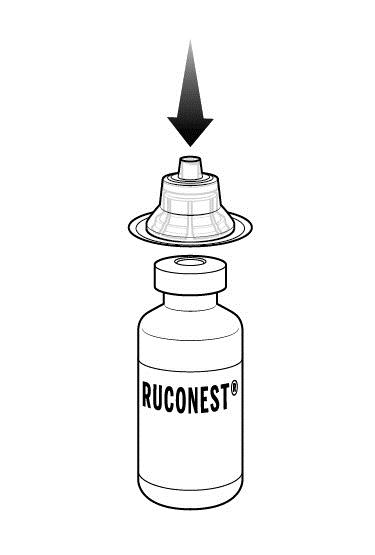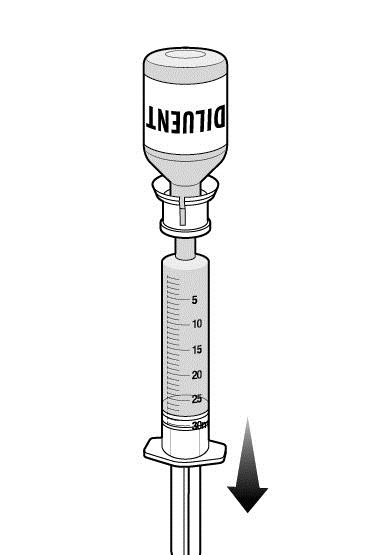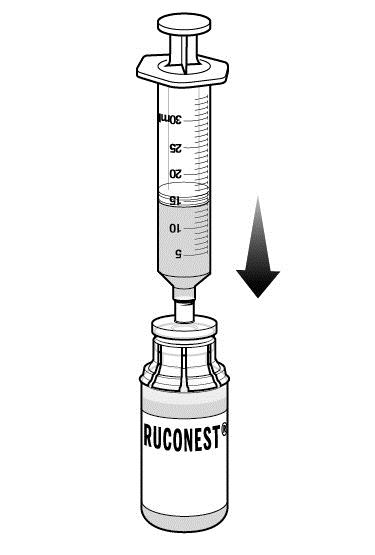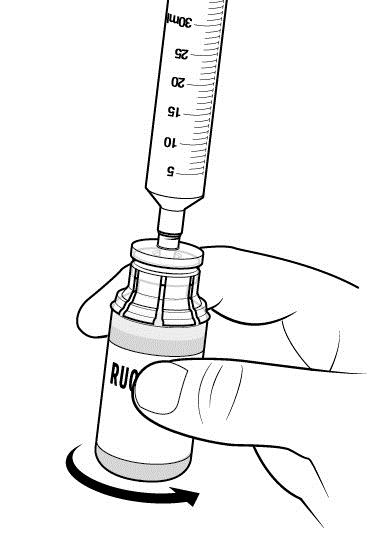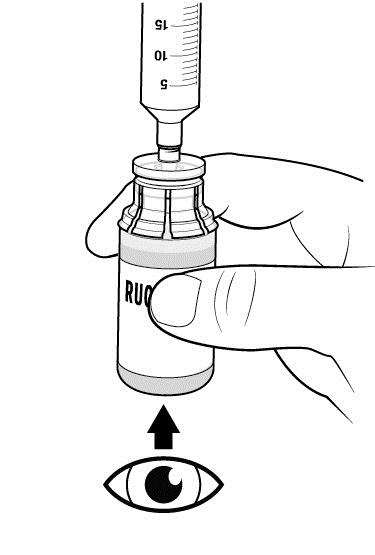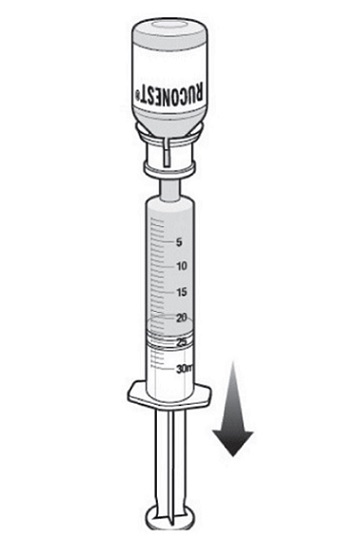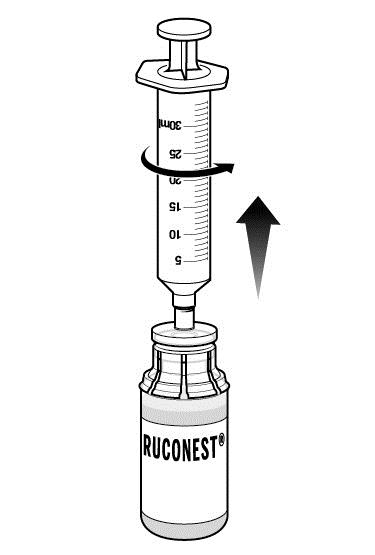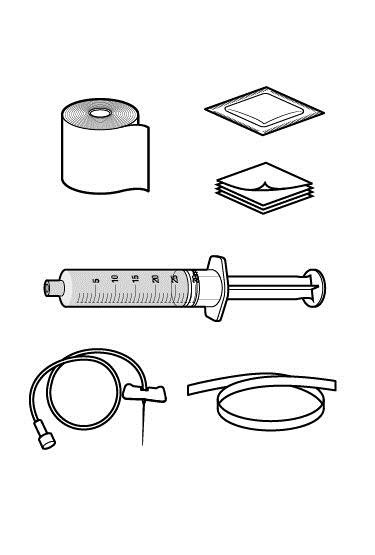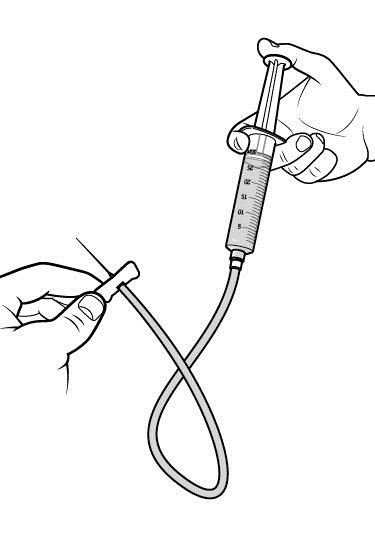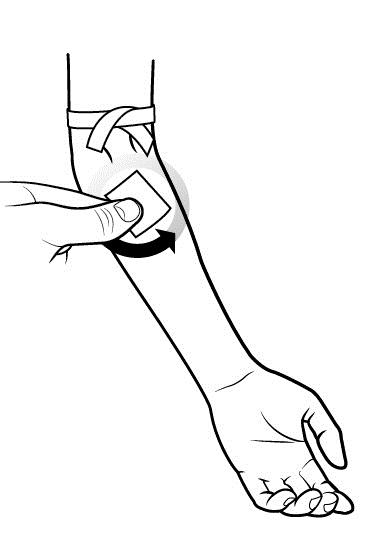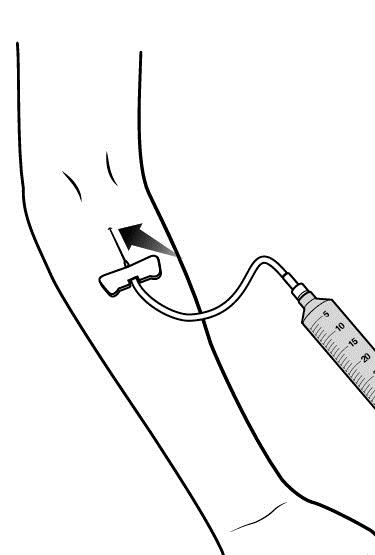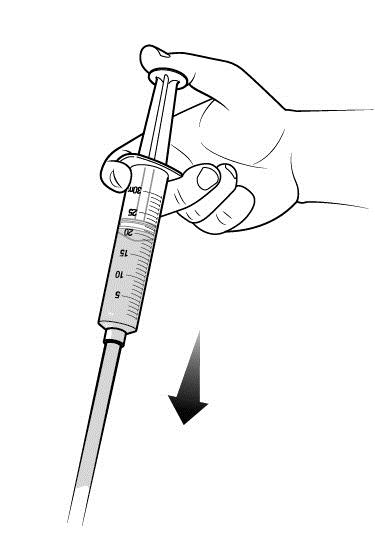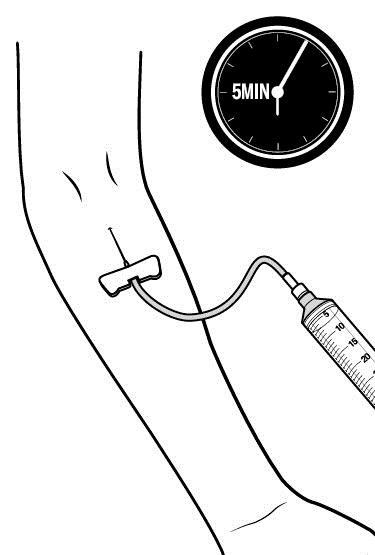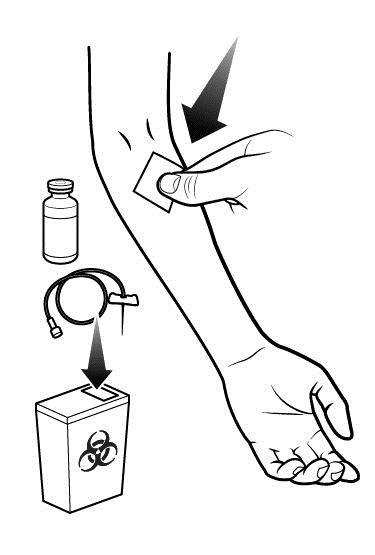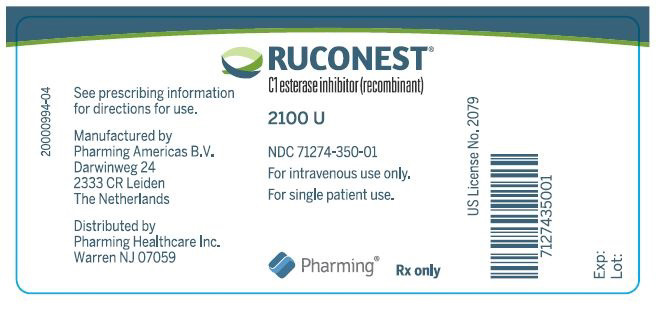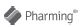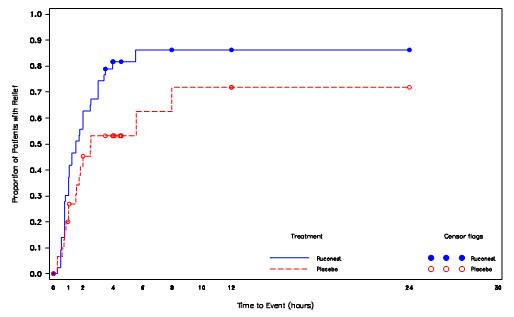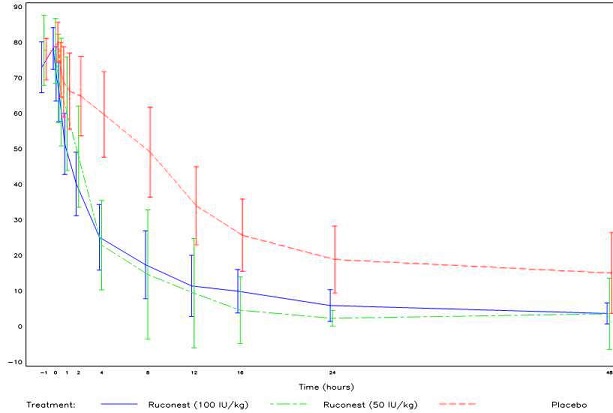 DRUG LABEL: Ruconest
NDC: 71274-350 | Form: INJECTION, POWDER, FOR SOLUTION
Manufacturer: Pharming Healthcare Inc.
Category: prescription | Type: HUMAN PRESCRIPTION DRUG LABEL
Date: 20200430

ACTIVE INGREDIENTS: CONESTAT ALFA 2100 U/1 1
INACTIVE INGREDIENTS: SUCROSE; SODIUM CITRATE, UNSPECIFIED FORM; CITRIC ACID MONOHYDRATE

HIGHLIGHTS OF PRESCRIBING INFORMATION

These highlights do not include all the information needed to use RUCONEST® safely and effectively. See full prescribing information for RUCONEST.
RUCONEST (C1 esterase inhibitor [recombinant])
For Intravenous Use, Lyophilized Powder For Reconstitution
Initial U.S. Approval: 2014

1 INDICATIONS AND USAGE

RUCONEST is a C1 esterase inhibitor [recombinant] indicated for the treatment of acute attacks in adult and adolescent patients with hereditary angioedema (HAE). (1)

Limitation of Use: Effectiveness was not established in HAE patients with laryngeal attacks.

2 DOSAGE AND ADMINISTRATION

For Intravenous Use Only.

- Reconstitute each vial (2100 U) by adding 14 mL sterile Water for Injection per vial to obtain a solution of 150 U per mL. (2.3)
- Administer the reconstituted solution at room temperature as a slow intravenous injection over approximately 5 minutes. (2.4)
- Appropriately trained patients may self-administer upon recognition of an HAE attack. (2.4)

Recommended dose of RUCONEST for an acute attack

Body weight | RUCONEST Dose for Intravenous Injection | Volume (mL) of Reconstituted Solution (150 U/mL) to be Administered
< 84 kg | 50 U per kg | Body weight in kg divided by 3
≥ 84 kg | 4200 U (2 vials) | 28 mL

If the attack symptoms persist, an additional (second) dose can be administered at the recommended dose level. Do not exceed 4200 U per dose. No more than two doses should be administered within a 24-hour period.

3 DOSAGE FORMS AND STRENGTHS

2100 U Lyophilized powder for reconstitution for injection in a single-use vial. (3)

4 CONTRAINDICATIONS

- Known or suspected allergy to rabbits and rabbit-derived products. (4)
- History of immediate hypersensitivity reactions, including anaphylaxis, to C1 esterase inhibitor preparations. (4)

5 WARNINGS AND PRECAUTIONS

- Hypersensitivity reactions, including anaphylaxis may occur. Should symptoms occur, discontinue RUCONEST and administer appropriate treatment. (5.1)
- Serious arterial and venous thromboembolic (TE) events have been reported at the recommended dose of plasma derived C1 esterase inhibitor products in patients with risk factors. Monitor patients with known risk factors for TE events during and after RUCONEST administration. (5.2)

6 ADVERSE REACTIONS

- The serious adverse reaction reported in clinical trials was anaphylactic reaction. (6)
- The common adverse reactions (≥ 2%) reported in clinical trials were headache, nausea, and diarrhea. (6)

To report SUSPECTED ADVERSE REACTIONS, contact Pharming Healthcare Inc. at 1-800-930-5221 or FDA at 1-800-FDA-1088 or www.fda.gov/medwatch.

FULL PRESCRIBING INFORMATION

1 INDICATIONS AND USAGE

RUCONEST is a C1 esterase inhibitor [recombinant] indicated for the treatment of acute attacks in adult and adolescent patients with hereditary angioedema (HAE).

Limitation of Use: Effectiveness was not established in HAE patients with laryngeal attacks.

2 DOSAGE AND ADMINISTRATION

For intravenous use after reconstitution only.

2.1 Recommended Dosing

- Training on how to administer RUCONEST should be conducted by a qualified healthcare professional experienced in the treatment of HAE.
- Appropriately trained patients may self-administer upon recognition of an HAE attack.
- The recommended dose of RUCONEST is 50 U per kg with a maximum of 4200 U to be administered as a slow intravenous injection over approximately 5 minutes.

If the attack symptoms persist, an additional (second) dose can be administered at the recommended dose level. Do not exceed 4200 U per dose. No more than two doses should be administered within a 24-hour period.

Table 1. Recommended dose of RUCONEST for an acute attack
Body Weight | RUCONEST Dose for Intravenous Injection | Volume (mL) of Reconstituted Solution (150 U/mL) to be Administered
< 84 kg | 50 U per kg | Body weight in kg divided by 3
≥ 84 kg | 4200 U (2 vials) | 28 mL

2.2 Preparation and Handling

- Store RUCONEST in the original carton and protect from light prior to reconstitution.
- Do not use after expiration date on the product vial label.
- Water for Injection is not included in the RUCONEST package.
- Use aseptic technique to reconstitute, mix the solution, and to combine the reconstituted solution from more than one vial (see Reconstitution [ 2.3] and Administration [ 2.4]).
- Do not mix or administer RUCONEST with other medicinal products or solutions.
- Discard all partially used vials after treatment.

2.3 Reconstitution

Each package contains one single-use vial of RUCONEST. To reconstitute, the following are also required:

- Sterile Water for Injection (diluent) - At least 14 mL per vial of RUCONEST requiring reconstitution.
- Antiseptic wipe
- Syringe
- Commercially available vial adapter and syringe luer lock or large bore needle. If using a syringe with vial adapter, use a new vial adapter for each vial of RUCONEST and diluent.

The procedures below are provided as general guidelines for the reconstitution and administration of RUCONEST.

- Ensure that the RUCONEST vial and diluent vial are at room temperature.
- Remove the flip caps from the RUCONEST and diluent vials. Treat the vial stoppers with the antiseptic wipe and allow to dry.
- Using the syringe/needle or syringe/vial adapter, withdraw 14 mL of sterile water for injection from the diluent vial.
- Remove the syringe and transfer the diluent to the RUCONEST vial. Add the diluent slowly to avoid forceful impact on the powder. Swirl the vial slowly to mix and avoid foaming.
- Repeat this procedure using another 14 mL of diluent and a second vial of RUCONEST.
- If the same patient is to receive more than one vial, the contents of multiple vials may be pooled into a single administration device (i.e., syringe).
- Inspect RUCONEST visually for particulate matter and discoloration after reconstitution and prior to administration. The reconstituted solution should be colorless, clear, and free from visible particles. Do not use if the solution is cloudy, colored, or contains particulates.
- RUCONEST vial is for single-use only.
- Use the reconstituted product immediately, or within 8 hours stored at 36ºF - 46ºF (2º - 8ºC). Discard partially used vials.
- Do not freeze the reconstituted solution.

2.4 Administration

- Do not mix RUCONEST with other medicinal products. Administer RUCONEST by a separate infusion line.
- Use aseptic technique when administering RUCONEST.
- Follow recommended venipuncture guidelines for initiating intravenous therapy.
- Administer RUCONEST by slow intravenous injection over approximately 5 minutes.
- For self-administration, provide the patient with instructions and training for intravenous injection outside of a clinic setting so patients may self-administer RUCONEST upon recognition of symptoms of an HAE attack [see Patient Counseling Information (17)].
- After administration, immediately discard any unused product and all used disposable supplies in accordance with local requirements.

3 DOSAGE FORMS AND STRENGTHS

- RUCONEST is available as a lyophilized powder for reconstitution for injection in a single-use 25 mL glass vial. Each vial contains 2100 U of rhC1INH.

4 CONTRAINDICATIONS

- RUCONEST is contraindicated in patients with a history of allergy to rabbits or rabbit-derived products.
- RUCONEST is contraindicated in patients with a history of life-threatening immediate hypersensitivity reactions to C1 esterase inhibitor preparations, including anaphylaxis.

5 WARNINGS AND PRECAUTIONS

5.1 Hypersensitivity

Severe hypersensitivity reactions may occur . The signs and symptoms of hypersensitivity reactions may include hives, generalized urticaria, tightness of the chest, wheezing, hypotension, and/or anaphylaxis during or after injection of RUCONEST. Should symptoms occur, discontinue RUCONEST and institute appropriate treatment. Because hypersensitivity reactions may have symptoms similar to HAE attacks, treatment methods should be carefully considered. [see Patient Counseling Information (17)]

5.2 Thromboembolic Events

Serious arterial and venous thromboembolic (TE) events have been reported at the recommended dose of plasma derived C1 esterase inhibitor products in patients with risk factors. Risk factors may include the presence of an indwelling venous catheter/access device, prior history of thrombosis, underlying atherosclerosis, use of oral contraceptives or certain androgens, morbid obesity, and immobility. Monitor patients with known risk factors for TE events during and after RUCONEST administration.

6 ADVERSE REACTIONS

The serious adverse reaction in clinical studies of RUCONEST was anaphylaxis.

The most common adverse reactions (≥ 2%) reported in all clinical trials were headache, nausea, and diarrhea.

6.1 Clinical Trials Experience

Because clinical trials are conducted under widely varying conditions, the adverse reaction rates observed in the clinical trials of a drug cannot be directly compared to rates in the clinical trials of another drug and may not reflect the rates observed in clinical practice.

The RUCONEST clinical development program evaluated a combined total of 940 administrations in 236 subjects (symptomatic and non-symptomatic). In clinical studies, a total of 205 symptomatic HAE patients received treatment with RUCONEST for a combined total of 650 acute angioedema attacks. Among these HAE patients, 83 were treated for a single HAE attack and 122 were treated for multiple attacks.

Three randomized, placebo-controlled clinical trials (RCTs) were conducted in which 137 patients experiencing acute HAE attacks received RUCONEST (either an initial 50 U/kg or 100 U/kg body weight dose) or placebo (saline solution).

Table 2 shows all adverse reactions (ARs) in the RCTs, compared with the placebo group.

Table 2. Adverse reactions occurring In ≥ 2% of subjects in the three RCT studies

MedDRA Preferred Term | RUCONEST; 100 U/kg; (N=29); n (%) | RUCONEST; 50 U/kg* (N=66) n (%) | Placebo**; (N=47) n (%)
Total number of patients with adverse reactions | 4 (14%) | 6 (9%) | 13 (28%)
Headache | 3 (10%) | 0 | 2 (4%)
Sneezing | 0 | 1 (2%) | 0
Angioedema | 1 (3%) | 0 | 0
Erythema marginatum | 0 | 1 (2%) | 0
Skin burning sensation | 0 | 1 (2%) | 0
Back pain | 0 | 2 (3%) | 0
C-reactive protein increased | 0 | 1 (2%) | 0
Fibrin D-dimer increased | 0 | 1 (2%) | 0
Vertigo | 1 (3%) | 0 | 0
Procedural headache | 0 | 1 (2%) | 0
Lipoma | 0 | 1 (2%) | 0

* Includes 5 patients who received an additional 50 U/kg dose
MedDRA: Medical Dictionary for Regulatory Activities, version 15.0.
** Events only occurring in placebo patients are not listed.
Integrated RCT and Open-Label Extension (OLE) Studies
In a total of seven RCT and OLE studies, 205 patients experiencing acute HAE attacks were treated with RUCONEST for a total of 650 HAE attacks. Included in this population were 124 patients who were treated at the 50 U/kg dosage strength for one or more attacks.

Table 3 shows adverse reactions in ≥ 2% of patients in any RUCONEST group for the integrated dataset combining all seven RCT and OLE studies in patients experiencing acute HAE attacks.

Table 3. Adverse reactions in the seven RCT and OLE studies occurring ≥ 2% of RUCONEST-treated patients (all doses), irrespective of causality

MedDRA Preferred Term | All RUCONEST doses* N=205 n (%)
Headache | 19 (9%)
Nausea | 5 (2%)
Diarrhea | 5 (2%)

* RUCONEST doses: doses up to 100 U/kg

MedDRA: Medical Dictionary for Regulatory Activities, version 15.0.

Immunogenicity
As with all therapeutic proteins, there is potential for immunogenicity. Pre- and post-exposure samples from 205 HAE patients treated for 650 acute attacks with RUCONEST were tested for the antibodies against plasma-derived C1INH or rhC1INH and for antibodies against host-related impurities (HRI). Testing was performed prior to and after treatment of a first attack and subsequent repeated attacks at 7, 22 or 28, and 90 days after RUCONEST treatment.

Prior to the first exposure to RUCONEST, the frequency of anti-C1INH antibodies varied from 1.2% to 1.6% of samples. After the first exposure, the frequency of anti-C1INH antibodies varied from 0.6% to 1.0% of samples tested. After repeated exposures, the frequency of anti-C1INH antibodies varied from 0.5 to 2.2% of samples tested. The frequency of anti-HRI antibodies was 1.0% in pre-exposure samples, and after the first exposure varied from 3.5% to 4.6%. After repeated exposure, the frequency of anti-HRI antibodies varied from 5.7% to 17% of samples. At least 10% of subjects formed a specific antibody response to RUCONEST after five treated HAE attacks. No anti-C1INH neutralizing antibodies were detected. Observed anti-C1INH and anti-HRI antibodies were not associated with adverse clinical findings.

The detection of antibody formation is highly dependent on the sensitivity and specificity of the assay. Additionally, the observed incidence of antibody (including neutralizing antibody) positivity in an assay may be influenced by several factors including assay methodology, sample handling, timing of sample collection, concomitant medications, and underlying disease. For these reasons, comparison of the incidence of antibodies to RUCONEST with the incidence of antibodies to other products may be misleading.

Postmarketing Experience
Because postmarketing reporting of adverse reactions is voluntary and from a population of uncertain size, it is not always possible to reliably estimate the frequency of these reactions or establish a causal relationship to product exposure.

Adverse reactions in HAE patients receiving RUCONEST include abdominal pain and rash.

8 USE IN SPECIFIC POPULATIONS

8.1 Pregnancy

Risk Summary

There are no adequate and well-controlled studies of RUCONEST in pregnant women. In the U.S. general population, regardless of drug exposure, available data suggest that major birth defects occur in 2 to 4% of the general population and miscarriage occurs in 15 to 20% of clinically recognized pregnancies.

Data

Human Data

Limited available postmarketing safety data with RUCONEST use in pregnant women do not indicate any adverse effects in this population. In a retrospective case collection study, 14 pregnant women aged 17 to 37 years with HAE received RUCONEST at 50 U/kg (max 4200 U) via intravenous administration for treatment of acute atttacks or for prophylaxis during pregnancy. For all 14 women in this study, delivery at full term with the births of healthy babies occurred without complications. No adverse events related to RUCONEST treatment were reported during the pregnancy period.^1,2 However these data cannot definitely establish the absence of any risk because of the small sample size and non-randomized study design.

Animal Data

Embryo toxicity with 625 U/kg of RUCONEST (12.5 times the human dose) was tested after intravenous dosing of pregnant rats in a segment II (embryofetal toxicity) study design. There were no significant outcomes from this study. Dosing of pregnant rabbits with 625 U/kg during organogenesis showed no drug-related adverse effects on either the developing fetuses or mothers [see Animal Toxicology and/or Pharmacology (13.2)].

8.2 Lactation

Risk Summary

There are no data on the presence of RUCONEST in human milk, its effects on the breastfed infant, or its effects on milk production. The developmental and health benefits of breastfeeding should be considered along with the mother's clinical need for RUCONEST and any potential adverse effects on the breastfed child from RUCONEST or from the underlying maternal condition.

8.4 Pediatric Use

The safety and efficacy of RUCONEST were evaluated in 17 adolescent patients (13-17 years of age) treated for 52 HAE attacks. Eight out of 17 (47%) adolescent patients experienced adverse reactions. No serious adverse reactions were reported in these patients. The most common reactions (occurring in at least 2 patients) were: abdominal pain, headache, and oropharyngeal pain.

8.5 Geriatric Use

The clinical studies of RUCONEST included seven patients older than 65 years. The clinical studies included an insufficient number of patients in this age group to determine if they respond differently from younger patients.

11 DESCRIPTION

RUCONEST is a recombinant analogue of human complement component 1 esterase inhibitor for intravenous injection. RUCONEST is purified from the milk of transgenic rabbits, and supplied as a sterile, preservative-free, white/off-white lyophilized powder for reconstitution for injection. One U of rhC1INH activity is defined as the equivalent of C1 esterase inhibiting activity present in 1 mL of pooled normal plasma.

RUCONEST is a soluble, single-chain glycoprotein containing 478 amino acids, with a molecular mass of 68 kDa, of which approximately 22% comprises oligosaccharide structures. The primary and secondary structures of the molecule and target protease selectivity are consistent with those of plasma-derived C1 esterase inhibitor.

Each vial of RUCONEST contains 2100 U of rhC1INH, 937 mg of sucrose, 83.3 mg of sodium citrate dihydrate and 1.0 mg of citric acid monohydrate. After reconstitution with 14 mL of sterile Water for Injection, each vial of RUCONEST contains 150 U of rhC1INH per 1 mL in a 20 mM sodium citrate buffer with a pH of 6.8. RUCONEST does not contain preservatives and each vial is for single use only.

RUCONEST is purified from the milk of transgenic rabbits. The rabbits are maintained in a closed colony that is controlled and routinely monitored for specific pathogens. The skimmed milk is screened for adventitious contaminants prior to further manufacture. The manufacturing process has been validated to demonstrate adequate capacity for removal and/or inactivation of viruses (Table 4). RUCONEST contains less than 0.002% of host-related impurities.

Table 4. Viral reduction capacity of the rhC1INH manufacturing process
 | Virus Reduction Factor (Log10)
Step | MLVa | REO 3 | ORF | FCV | PPV
SP BB chromatographyb | 1.8 | 2.2c | 1.5c | 2.3 | 1.5b
SD incubationb | ≥ 5.8 | NAd | 3.7 | NA | NA
Q HP chromatographyb | NTe | 4.8 | NT | 0.8c | 2.2
Zn FF chromatographyb | 1.1c | 3.2c | 3.3 | 1.9c | 0.4c
Nanofiltration | ≥ 5.5 | ≥ 6.5 | ≥ 5.8 | ≥ 6.9 | 5.8
Total reduction factor | ≥ 13.1 | ≥ 11.3 | ≥ 12.8 | ≥ 9.2 | 8.0
a MLV: Murine leukemia virus; REO-3: Reovirus type 3; ORF: Scab-mouth ORF virus; FCV: Feline calicivirus; PPV: Porcine parvovirus;
b SP BB: SP Sepharose BB; SD: Solvent/detergent; Q HP: Q Sepharose HP; Zn FF: Zinc Chelating Sepharose FF;
c Not added to the total reduction factor since independence of clearance mechanism has not been experimentally verified;
d Not applicable since indicated model virus is not enveloped;
e Not tested because SD chemicals are present in the starting material.

12 CLINICAL PHARMACOLOGY

12.1 Mechanism of Action

C1 esterase inhibitor (C1INH) is a normal constituent of human blood and is one of the serine protease inhibitors (serpins). The primary function of C1INH is to regulate the activation of the complement and contact system pathways. Regulation of these systems is performed through the formation of complexes between the protease and the inhibitor, resulting in inactivation of both and consumption of the C1INH.

C1INH exerts its inhibitory effect by irreversibly binding several proteases (target proteases) of the contact and complement systems. The effect of RUCONEST on the following target proteases was assessed in vitro: activated C1s, kallikrein, factor XIIa and factor XIa. Inhibition kinetics were found to be comparable with those observed for plasma-derived human C1INH.

HAE patients have low levels of endogenous or functional C1INH. Although the events that induce attacks of angioedema in HAE patients are not well defined, it is thought that contact system activation, and resulting increased vascular permeability lead to the clinical manifestation of HAE attacks. Suppression of contact system activation by C1INH through the inactivation of plasma kallikrein and factor XIIa is thought to modulate vascular permeability by preventing the generation of bradykinin.^3

Administration of RUCONEST increases plasma levels of functional C1INH activity.

12.2 Pharmacodynamics

The complement component (protein) C4 is a substrate for activated C1. Patients with HAE have low levels of C4 in the circulation; RUCONEST shows a dose-dependent restoration of complement homeostasis of C4 in HAE patients. A dose of 50 U/kg of RUCONEST increases plasma C1INH activity levels to greater than 0.7 U/mL (the lower limit of normal) in HAE patients.

12.3 Pharmacokinetics

The pharmacokinetics of RUCONEST was evaluated in a study of 12 asymptomatic HAE patients (dose ranged from 6.25 U/kg to 100 U/kg). Pharmacokinetics evaluation was performed by non-compartmental analysis, using functional C1INH levels. Following administration of RUCONEST (50 U/kg) in asymptomatic HAE patients (Table 5), the mean Cmax was 1.2 U/mL, and the elimination half-life was approximately 2.5 hours. The clearance of RUCONEST was nonlinear (clearance decreased with increasing dose) over the dose range of 25-100 U/kg.

Table 5. Baseline corrected pharmacokinetic parameters (Mean ± SD) of functional C1INH following administration of 50 U/kg and 100 U/kg RUCONEST to asymptomatic HAE patients
Parameters | 50 U/kg | 100 U/kg
Cbaseline (U/mL) | 0.18 ± 0.12 | 0.14 ± 0.08
Cmax (U/mL) | 1.2 ± 0.2 | 2.3 ± 0.2
Tmax (hours) | 0.31 ± 0.10 | 0.31 ± 0.10
AUC (U x hr/mL) | 3.3 ± 1.0 | 10.6 ± 2.5
CL (mL/hr) | 1207 ± 414 | 781 ± 147
Half-life (hours) | 2.4 ± 0.6 | 2.7 ± 0.3
Vss (L) | 3.0 ± 0.9 | 2.4 ± 0.5

Studies have not been conducted to evaluate the PK of RUCONEST in special patient populations, identified by race, age (pediatric or geriatric), or the presence of renal or hepatic impairment.

13 NONCLINICAL TOXICOLOGY

13.1 Carcinogenesis, Mutagenesis, Impairment of Fertility

No animal studies have been conducted to evaluate the effects of RUCONEST on carcinogenesis and mutagenesis. Fertility was not evaluated in animal studies.

13.2 Animal Toxicology and/or Pharmacology

Single- and repeat-dose studies of up to 14 days in rats, dogs, and cynomolgus monkeys with daily doses of RUCONEST up to 80 times the human dose (50 U/kg) were conducted. In a 14-day monkey toxicology study of intravenous doses up to 2000 U/kg twice daily, increases in AST and ALP were observed at doses of 500 U/kg and higher. No histopathological correlates were observed in the liver and the increases in liver enzymes were reversible. Histologic findings included changes in the size of thymic cortex and medulla, and microvacuoles in the epithelial cells lining the renal tubules. The renal tubular vacuolation was dose dependent, but was not accompanied by other histological changes in the kidney. This finding was only partially reversible at the highest dose level of 2000 U/kg twice daily. It was concluded that the NOAEL of RUCONEST was 1000 U/kg twice daily in this species. There were no adverse findings in a safety pharmacology study in dogs and a local tolerance study in rabbits. It is concluded that preclinical toxicology data for daily doses up to 40 times the proposed human dose of RUCONEST (50 U/kg) do not indicate a safety concern for the use of RUCONEST in humans.

Embryo-fetal studies have been conducted in rabbits and rats at a dose of RUCONEST 12.5 times the human dose of 50 U/kg. In rats, no malformed fetuses were observed. In rabbits, an increase in the incidence of fetal cardiac vessel defects was observed (1.12% [2 cases] in the treatment group compared to 0.03% in historical controls). These defects are considered to be a chance finding, but a RUCONEST-related effect cannot be excluded.

14 CLINICAL STUDIES

The safety and efficacy of RUCONEST for treatment of acute angioedema attacks in patients with HAE was established in Study 1, a double-blind, randomized, placebo-controlled trial (RCT) which included an open-label extension (OLE) phase; and supported by the results of 2 additional RCTs and 2 additional OLE studies.

Randomized, Controlled Trials

The safety and efficacy of RUCONEST in the treatment of acute attacks in patients with hereditary angioedema were demonstrated in a placebo-controlled, double-blind, randomized study (Study 1). Supportive evidence of effectiveness is provided by two double-blind, randomized, placebo-controlled studies (Studies 2 and 3). Evidence for the efficacy of repeat treatment of HAE attacks is provided from the open-label extensions (OLE) of each of the three randomized studies.

Study 1 was a randomized, double-blind, placebo-controlled trial that included an open-label extension (OLE) phase to assess the efficacy and safety of RUCONEST 50 U/kg in the treatment of acute attacks in patients with HAE. Seventy-five (75) adults and adolescent patients were randomized (3:2) to receive RUCONEST 50 U/kg (N = 44) or placebo (N = 31). Patients ranged in age from 17 to 69 years of age; 63% were female and 37% were male; 96% were Caucasian.

The primary efficacy endpoint was the time to beginning of relief of symptoms, assessed using patient-reported responses to two questions from a Treatment Effect Questionnaire (TEQ). The TEQ required patients to assess the severity of their attack symptoms at each affected anatomic location, using a seven-point scale (“much worse” to “much better” [TEQ Question 1]), and whether their symptoms had begun to decrease notably since receiving the study medication (“yes” or “no” [TEQ Question 2]). To achieve the primary endpoint, a patient had to have a positive response to both questions along with persistence of improvement at the next assessment time (i.e., the same or better response).

Rescue treatment with RUCONEST was available for patients who did not experience the beginning of relief at 4 hours after study drug administration, or earlier to patients who experienced life-threatening oropharyngeal-laryngeal angioedema symptoms. If a patient received a medication which could have impacted the efficacy evaluation or open-label RUCONEST as rescue medication, prior to achieving beginning of relief of symptoms, the time to beginning of relief of symptoms was censored at the last assessed time prior to medication use.

In the RCT phase, the median time to beginning of relief of symptoms was statistically significantly shorter in patients treated with RUCONEST 50 U/kg compared with patients treated with placebo as assessed by the TEQ; (Table 6, Figure 1).

Table 6. Time to Beginning of Relief of Symptoms based on questionnaire based on TEQ (Study 1, RCT Phase)
Time to Beginning of Relief of Symptoms, minutes | RUCONEST 50 U/kg N=44 | Placebo N=31
Median | 90 | 152
95% CI | (61, 150) | (93, -)
Log-rank p-value | 0.031
Values that are not estimable are displayed as ‘- ’.

Figure 1. Kaplan-Meier Plot of Time to Beginning of Relief of Symptoms (Study 1, RCT Phase)

Among several planned subgroup analyses, descriptive statistics showed that in US patients a median time to beginning of relief of symptoms with persistence at the primary attack location (based on TEQ) was 98 minutes [95% CI:(45, 240); n=22] for those receiving RUCONEST and 90 minutes [95% CI: (50, -); n=16] for those receiving placebo. The hazard ratio for time to the beginning of relief of symptoms in this subpopulation was 1.20 [95% CI: (0.48, 3.01)] for patients receiving RUCONEST as compared with patients receiving placebo. Non-US patients receiving RUCONEST had a median time to beginning of relief of 90 minutes [95% CI: (63, 120); n=22] and non-US patients receiving placebo had a median time to beginning of relief of 334 minutes [95% CI: (150, -); n=15]. The hazard ratio for the non-US subgroup was 4.82 [95% CI: (1.58, 14.72)] for patients receiving RUCONEST compared to placebo.

Examination of gender subgroups suggested a larger treatment effect in men than women. For women receiving RUCONEST, the median time to beginning of relief was 113 minutes [95% CI: (63, 151); n=28], and for women receiving placebo, the median time to beginning of relief was 105 minutes [95% CI: (60, 334); n=19]. The hazard ratio for women receiving RUCONEST versus placebo was 1.22 [95% CI: (0.60, 2.48)]. For men receiving RUCONEST, the median time to beginning of relief was 75 minutes [95% CI: (45, 210); n=16], and for men receiving placebo, the median time to beginning of relief was 480 minutes [95% CI: (150, -) n=12]. The hazard ratio for men receiving RUCONEST versus placebo was 3.94 [95% CI: (1.23, 12.68)].

No plausible biological explanations for the regional or gender subgroup effects were found. One possible explanation is a larger-than-expected placebo response among US women. None of the subgroup confidence intervals were adjusted for multiplicity.

Because almost all of the patients were Caucasian and were between 18 and 65 years of age, race and age subgroup analyses were not considered meaningful.

Among patients who achieved relief within 4 hours, there were 4 (27%) patients in the placebo group who had a relapse of their symptoms within 24 hours as compared with 1 (3%) in the RUCONEST group. The proportion of patients who received RUCONEST as rescue medication was greater in patients randomized to placebo (13 of 31 patients; 42%) than in patients randomized to RUCONEST (5 of 44 patients; 11%).

The efficacy of RUCONEST 50 U/kg for different anatomical locations of HAE attacks is summarized in Table 7.

Table 7. Proportion of patients who achieved relief within 4 hours, by attack type
Attack Type* | RUCONEST 50 U/kg; n/N (%) | Placebo; n/N (%)
Abdominal | 14/16 (88%) | 7/12 (58%)
Facial | 3/6 (50%) | 0/2 (0%)
Peripheral (extremities) | 17/20 (85%) | 7/14 (50%)
*Life-threatening laryngeal attacks were excluded from the randomized-controlled phase of Study 1

In the OLE phase of Study 1, patients were treated with open-label RUCONEST 50 U/kg for repeated attacks of HAE. Forty-four patients who completed the RCT phase were enrolled into the OLE phase where they were treated for a total of 170 attacks. In this phase, the median time to beginning of relief of symptoms was 75 minutes [95% CI: (64, 90)], consistent with the results of the RCT phase of the study (Table 6). Results were also comparable across attacks, suggesting that the efficacy of RUCONEST 50 U/kg was maintained over repeated attacks of HAE. In the OLE phase of Study 1, 5/170 (3%) attacks received a second dose of RUCONEST 50 U/kg.

In Study 2 (North American RCT), patients were randomized to receive a single administration of either RUCONEST 50 U/kg (N=12), RUCONEST 100 U/kg (N=13) or placebo (N=13). Patients ranged in age from 17 to 66 years of age; 74% were female and 26% were male; and 92% were Caucasian.

In Study 3 (European RCT), patients were randomized to receive a single administration of either RUCONEST 100 U/kg (N=16) or placebo (N=16). Patients ranged in age from 17 to 71 years of age: 53% were female and 47% were male; and 100% were Caucasian.

Patients scored their symptoms using a visual analog scale (VAS) ranging from 0-100 mm. A VAS decrease of > 20 mm compared with baseline with persistence of the improvement at two consecutive time points was considered the onset of relief in Studies 2 and 3.

In both Study 2 and 3, the efficacy of RUCONEST in the treatment of acute angioedema attacks was demonstrated by significantly shorter times to beginning of relief of symptoms based on the VAS (Figure 2).

Figure 2. Mean VAS scores over time with 95% Confidence Intervals (Study 2 and 3, RCT Phase)

In open-label extension studies of Study 2 and 3, 119 patients were treated with RUCONEST for a total of 362 acute angioedema attacks. As observed in Study 1, the efficacy of RUCONEST was maintained for repeat attacks.

15 REFERENCES

1. Moldovan D, Bernstein JA, Hakl R, Porebski G, Poarch K, Lumry WR, Relan A. Safety of recombinant human C1 esterase inhibitor for hereditary angioedema attacks during pregnancy. J Allergy Clin Immunol Pract. 2019 Jun 3. pii: S2213-2198(19)30499-4.
2. Hakl R, Kuklinek P, Krcmova I, Kralickova P, Freiberger T, Janku P, Vlkova M, Litzman J. Treatment of hereditary angioedema attacks with icatibant and recombinant C1 inhibitor during pregnancy. J Clin Immunol. 2018 Oct;38(7):80-815.
3. Caliezi C, Wuillemin WA, Zeerleder S, Redondo M, Eisele B, Hack CE. C1-esterase inhibitor: an anti-inflammatory agent and its potential use in the treatment of diseases other than hereditary angioedema. Pharmacol Rev. 2000 Mar;52(1):91-112.

16 HOW SUPPLIED/STORAGE AND HANDLING

16.1 How Supplied

- RUCONEST is supplied in single-use 25 mL glass vials with a stopper (siliconized chlorobutyl rubber) and a flip-off seal (aluminum and colored plastic).
- Each carton contains one single-use vial.
- Each vial contains 2100 U rhC1INH lyophilized powder for reconstitution for injection.

16.2 Storage and Handling

- Store in the original package in order to protect from light.
- Shelf life: 48 months when stored at 36ºF - 77ºF (2ºC - 25ºC).
- Do not freeze.
- Each vial of RUCONEST should be reconstituted with 14 mL Water for Injection (not supplied). The reconstituted solution contains 150 U/mL rhC1INH and is clear and colorless.
- Each vial of RUCONEST is for single use only. RUCONEST contains no preservative. Any product that has been reconstituted should be used immediately, or within 8 hours stored at 36ºF - 46ºF (2ºC - 8ºC). Discard partially used vials after treatment.

17 PATIENT COUNSELING INFORMATION

Advise the patient to read the FDA-Approved patient labeling (Product Information and Instructions for Use).

Patients being treated with RUCONEST should receive the following information and instructions. This information is intended to aid the patient in the safe and effective use of RUCONEST.

- Advise female patients to notify their physician if they are pregnant or intend to become pregnant during the treatment of acute attacks of HAE with RUCONEST.

- Advise patients to notify their physician if they are breastfeeding or plan to breastfeed.

- Inform patients of the risks and benefits of RUCONEST before prescribing or administering it to the patient.

Advise patients to immediately report :

- Signs and symptoms of allergic hypersensitivity reactions, such as hives, urticaria, tightness of the chest, wheezing, hypotension and/or anaphylaxis experienced during or after injection of RUCONEST [ see WARNINGS AND PRECAUTIONS/Hypersensitivity (5)].

Manufactured by:
Pharming Americas B.V.
Darwinweg 24
2333 CR Leiden
The Netherlands
RUCONEST® is a registered trademark of Pharming Intellectual Property B.V.

Distributed by:
Pharming Healthcare Inc.

Warren NJ 07059

Product protected by U.S patent Nos. 7,067,713 and RE43691.

Please see www.ruconest.com for patent information.

US License No. 2079

FDA-Approved Patient Labeling - Patient Product Information (PPI)

RUCONEST® (ROO-Ko-nest)

(C1 esterase inhibitor [recombinant])

Lyophilized powder for reconstitution for injection in a single-use vial

This leaflet summarizes important information about RUCONEST. Please read it carefully each time before using RUCONEST. There may be new information provided. This information does not take the place of talking with your healthcare provider, and it does not include all of the important information about RUCONEST. If you have any questions after reading this, ask your healthcare provider.

What is RUCONEST?

RUCONEST is an injectable medicine that is used to treat acute angioedema attacks in adult and adolescent patients with Hereditary Angioedema (HAE). HAE is caused by a shortage of a protein called C1 esterase inhibitor, that is present in your blood and helps control inflammation (swelling) and parts of the immune system. A shortage of C1 esterase inhibitor can lead to repeated attacks of swelling, pain in the abdomen, difficulty breathing and other symptoms. RUCONEST contains C1 esterase inhibitor.

Who should not use RUCONEST?

You should not use RUCONEST if you have a known or suspected allergy (hypersensitivity) to rabbits or rabbit-derived products.

You should not use RUCONEST if you have experienced life-threatening immediate hypersensitivity reactions, including anaphylaxis, to RUCONEST or to any other C1 esterase inhibitor product.

RUCONEST is not indicated for use in children under the age of 13 years.

What should I tell my healthcare provider before using RUCONEST?

Tell your healthcare provider about all of your medical conditions, including if you:

- have an allergy to rabbits since this can put you at high risk of a serious allergic reaction with RUCONEST. These allergy symptoms could include runny nose, itchy nose, sneezing, coughing, wheezing, difficulty breathing or watery eyes when you are near rabbits.
- are pregnant or planning to become pregnant. It is not known if RUCONEST can harm your unborn baby.
- are breastfeeding or plan to breastfeed. It is not known if RUCONEST passes to your milk and if it can harm your baby.

Tell your healthcare provider and pharmacist about all of the medicines you take, including all prescription and non-prescription medicines such as over-the-counter medicines, supplements, or herbal remedies.

How is RUCONEST given?

RUCONEST will be slowly injected into your vein (intravenous injection). Before injection, the RUCONEST powder must be dissolved using sterile Water for Injection. The dose will be determined based on your weight.

Most of the time a single dose of RUCONEST is enough to treat an attack, but a second dose may be needed.

What are the possible side effects of RUCONEST?

Like all medicines, RUCONEST can cause side effects, although not everybody gets them.

Allergic reactions may occur with RUCONEST. Call your healthcare provider or the emergency department immediately if you have any of the following symptoms after receiving RUCONEST:

- wheezing
- difficulty breathing
- chest tightness
- turning blue (look at lips and gums)
- fast heartbeat
- swelling
- faintness
- rash
- hives

In clinical studies, the most severe side effect reported in a person who received RUCONEST was a severe allergic reaction in a subject who was allergic to rabbits.

Other side effects patients experienced during clinical research studies include:

- headache
- nausea
- diarrhea

These are not all the possible side effects of RUCONEST.

If any of the side effects get serious, or if you notice any side effects not listed in the leaflet, please inform your healthcare provider or pharmacist. You can also report side effects to the FDA at 1-800-FDA-1088 or www.fda.gov/medwatch or contact Pharming Healthcare Inc. at 1-800-930-5221.

You can ask your healthcare provider for information about RUCONEST that is written for healthcare providers.

General Information about RUCONEST

Do not use RUCONEST for a condition for which it is not prescribed.

If you would like more information, talk to your healthcare provider. You can ask your healthcare provider or pharmacist for information about RUCONEST that was written for healthcare professionals.

For more information go to www.ruconest.com or call 1-800-930-5221.

RECOMMENDED PREPARATION OF MEDICATION AND MATERIALS

Use aseptic (sterile) technique when preparing and administering RUCONEST.

Step 1: Assemble supplies from medication box on a clean flat surface.

- 2 single-use vials of RUCONEST
- Sterile Water for Injection (diluent), 14mL per vial of RUCONEST to be reconstituted.
- Antiseptic wipes
- 1 syringe, 30 mL
- Needle-free, vented or non-vented vial adapters (or large bore needle). Use a new vial adapter for each vial of RUCONEST and diluent.

Step 2: Inspect the RUCONEST vial. Do not use if:

- The protective cap is missing
- The expiration date (see label) has passed

Step 3: Wash hands.

- Thoroughly wash and dry your hands

DOSAGE VERIFICATION

Discuss this section with your healthcare provider to ensure that the correct dose of RUCONEST is administered.

- The dose of RUCONEST and volume (mL) of reconstituted solution to be administered is based on body weight show in the chart below. No more than 2 vials may be combined for a single dose.

Body weight | RUCONEST dose for intravenous injection | Volume (mL) of reconstituted solution (150 U/mL) to be administered
<84 kg (185.2 lb) | 50 U per kg of body weight | Body weight in kg divided by 3
≥84 kg (185.2 lb) | 4200 U (2 vials) | 28 mL

RECONSTITUTION

The procedures below are provided as general guidelines for the reconstitution of RUCONEST.

Step 1: Ensure that the RUCONEST vials and the diluent vial are at room temperature (range of 68°F - 77°F or 20°C - 25°C).

The RUCONEST vial is for single

Step 2: Place the 2 RUCONEST vials and the diluent vial on a flat surface and remove the flip caps on each vial

- Wipe the vial stoppers with the antiseptic wipes provided and allow to dry for 30 seconds.
- Do not blow on the stoppers after wiping.
- Do not touch the stopper with your hands, or allow it to touch any surface.

Step 3: Peel back the covers from the clear plastic vial adapter packages.

- Leave the adapters in their packages.

Step 4: While holding the adapter in its package, place the first adapter over the diluent vial and press down until the device snaps into place.

- Leave the package on the adapter until you are ready to attach the syringe.

Step 5: Now, place a 2nd adapter over a RUCONEST vial and press down until it snaps into place.

Repeat if your dose requires a 2nd RUCONEST vial.

Step 6: Lift the package away from the diluent adapter.

Step 7: Remove syringe from package and withdraw sterile water for injection from the diluent vial.

- With vial on a flat surface, attach syringe to adapter on diluent vial by rotating syringe clockwise.
- Turn diluent vial upside down and slowly withdraw either 14 mL (if using 1 RUCONEST vial) or 28 mL (if using 2 RUCONEST vials) of diluent into syringe by gently pulling back on the plunger.
- There will still be some diluent left in the vial.
- Place the diluent vial back on a flat surface and detach syringe by gently pulling the syringe and rotating counterclockwise.

Step 8: Transfer the diluent to the RUCONEST vial.

- Remove the package from the adapter connected to one of the RUCONEST vials.
- Attach the syringe holding the diluent to the adapter on the RUCONEST vial by inserting the tip into the adapter opening while firmly pushing and rotating the syringe clockwise.
- Slowly press 14 mL of diluent into the RUCONEST vial.
- Add the diluent slowly to avoid forceful impact on the powder.
- Note: Leave the syringe attached to the vial after adding the diluent.

Step 9: Swirl the vial to mix. Do this slowly to avoid foaming.

Repeat Steps 8 and 9 if you are using a second RUCONEST vial. Remove syringe from the first RUCONEST vial prior to attaching to the second vial.

Step 10: Inspect RUCONEST vial(s) visually.

- After reconstitution and prior to administration, inspect the RUCONEST vials visually for particulate matter and discoloration.
- The reconstituted solution should be colorless, clear, and free from visible particles.
- Do not use the vial if it looks cloudy, contains particles, or has changed color.

Step 11: With the syringe still connected to the RUCONEST vial, turn the vial upside down.

- Slowly withdraw your dose of RUCONEST by gently pulling back on the plunger.
- Once you have withdrawn your dose, turn the vial right side up and place on a flat surface. Disconnect the syringe by gently pulling and rotating counterclockwise.

Step 12: Repeat Step 11 and withdraw additional reconstituted RUCONEST from the second RUCONEST vial (if needed).

- Withdraw only as much as is needed based on your body weight.
- Disconnect the syringe, for use as described in the next section.

SELF-ADMINISTRATION (intravenous injection)

Your healthcare provider will teach you how to safely administer RUCONEST. It is important that you inject RUCONEST directly into a visible vein. Do not inject into surrounding tissues or an artery. Once you learn how to self-administer, follow the instructions provided below. The reconstituted solution should be used within 8 hours and should be cooled but not be frozen.

Step 1: Assemble supplies.

- Gather the RUCONEST syringe, the following disposable supplies (not provided with RUCONEST), and other items:
  - Standard butterfly catheter infusion set (IV administration set with winged adapter and needle)
  - Sterile syringe
  - Tourniquet
  - Sterile gauze and tape or transparent dressing
  - Bandage (adhesive dressing)
  - Gloves (if recommended by your healthcare provider)
  - Antiseptic wipe for cleaning skin
- Other items (not shown)
- Clock or stopwatch to monitor time
- Sharps or other disposal container
- Treatment diary

Step 2: Clean surface.

- Thoroughly clean a table or other flat surface using one or more of the antiseptic wipes.

Step 3: Prime the infusion set.

As instructed by your healthcare provider:

- To prime (fill) the infusion tubing, connect the syringe filled with RUCONEST to the infusion set tubing and gently push on the syringe plunger to fill the tubing with RUCONEST.

Step 4: Prepare the approved IV injection site.

- Apply a tourniquet above the site of the infusion.
- Prepare the injection site by wiping the skin well with an antiseptic wipe, beginning at the center and working outward in a circular motion.
- Allow the site to dry.

Step 5: Start infusion.

Follow the instructions provided by your healthcare provider.

- Take off the needle sheath.
- Hold both wings of the butterfly between the thumb and the index finger with the obliquely cut (slanted) opening of the butterfly needle pointing upward.
- Insert the butterfly needle of the infusion set into your vein (insert as flat to skin surface as possible).
- Use sterile gauze and tape or transparent dressing to hold the needle in place.
- Make sure the needle is in a vein:
  - Gently pull back on the syringe plunger and check to see if blood is in the tubing.
  - If there is blood present, then the needle is in a vein.
  - If there is no blood, remove the needle and repeat this step using a new needle, new administration tubing, and a different injection site.
- Remove the tourniquet.
- Note: Inject RUCONEST slowly over approximately 5 minutes.

Step 6: Cover the injection site and clean up.

After all of the RUCONEST has been infused:

- Withdraw the butterfly needle along the line that it was inserted.
- Cover the injection site with a bandage, holding pressure on the site for a few minutes.
- Dispose of all unused solution, empty vials, and used needles and syringe in an appropriate container used for medical waste.

POST-ADMINISTRATION

The procedures below are provided as general guidelines for after the infusion of RUCONEST.

Record each injection into treatment journal.

- Record the lot number from the RUCONEST vial label.
- Enter the date and time of your injection.

This Patient Package Insert has been approved by the US Food and Drug Administration.

Manufactured by:

Pharming Americas B.V.

Darwinweg 24

2333 CR Leiden

The Netherlands

RUCONEST® is a registered trademark of Pharming Intellectual Property B.V.

Distributed by:

Pharming Healthcare Inc.

Warren NJ 07059

Product protected by U.S. patent Nos. 7,067,713 and RE43691.

Please see www.ruconest.com for patent information.

US License No. 2079

Revised: APR 2020

Package Label/Principal Display Panel - 2100 U Vial Label

RUCONEST®

C1 esterase inhibitor (recombinant)

2100 U

NDC 71274-350-01

For intravenous use only.

For single patient use.

See prescribing information for directions for use.

Rx only

Package Label/Principal Display Panel - 2100 U Carton

RUCONEST®

C1 esterase inhibitor (recombinant)

2100 U

NDC 71274-350-02

For intravenous use only.

For single patient use.

See prescribing information for directions for use.

Rx only